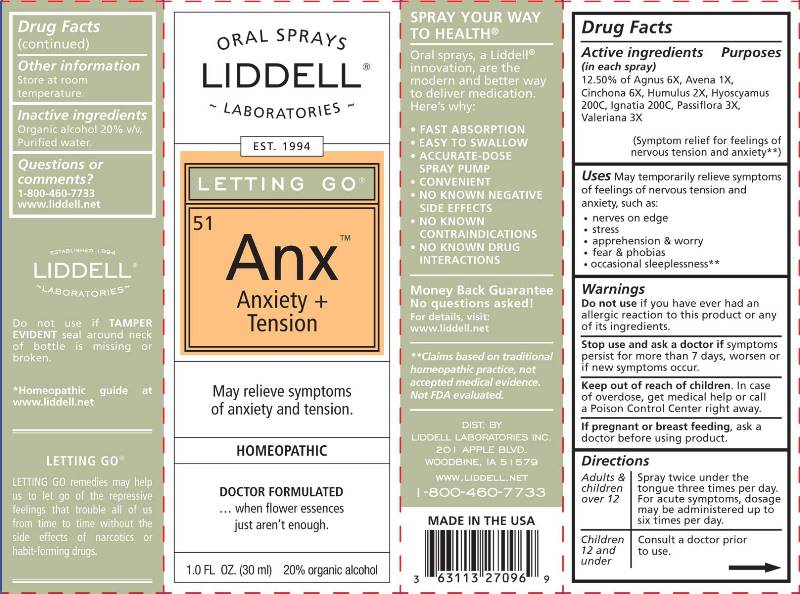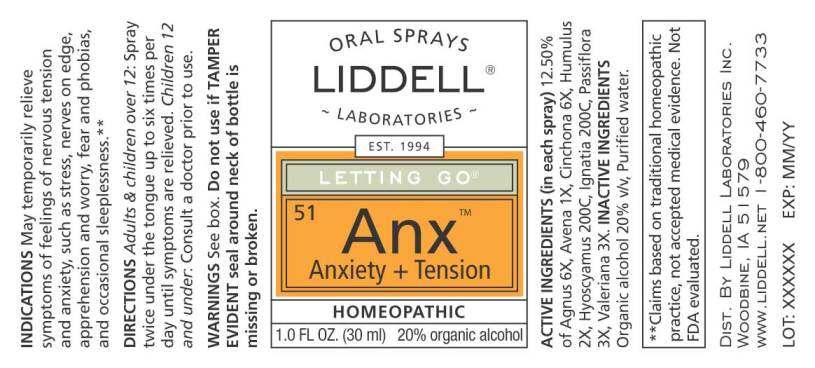 DRUG LABEL: Anxiety plus Tension
NDC: 50845-0047 | Form: SPRAY
Manufacturer: Liddell Laboratories, Inc.
Category: homeopathic | Type: HUMAN OTC DRUG LABEL
Date: 20180820

ACTIVE INGREDIENTS: CHASTE TREE 6 [hp_X]/1 mL; AVENA SATIVA FLOWERING TOP 1 [hp_X]/1 mL; CINCHONA OFFICINALIS BARK 6 [hp_X]/1 mL; HOPS 2 [hp_X]/1 mL; HYOSCYAMUS NIGER 200 [hp_C]/1 mL; STRYCHNOS IGNATII SEED 200 [hp_C]/1 mL; PASSIFLORA INCARNATA TOP 3 [hp_X]/1 mL; VALERIAN 3 [hp_X]/1 mL
INACTIVE INGREDIENTS: WATER; ALCOHOL

Drug Facts:

ACTIVE INGREDIENTS:

(in each spray) 12.50% of Agnus Castus 6X, Avena Sativa 1X, Cinchona Officinalis 6X, Humulus Lupulus 2X, Hyoscyamus Niger 200C, Ignatia Amara 200C, Passiflora Incarnata 3X, Valeriana Officinalis 3X.

USES:

May temporarily relieve symptoms of feelings of nervous tension and anxiety such as:

- nerves on edge
- stress
- apprehension & worry
- fear & phobias
- occasional sleeplessness**

**Claims based on traditional homeopathic practice, not accepted medical evidence. Not FDA evaluated.

WARNINGS:

Do not use if you have ever had an allergic reaction to this product or any of its ingredients.

Stop use and ask a doctor if symptoms persist, worsen or if new symptoms occur.

Keep out of reach of children. In case of overdose, get medical help or call a Poison Control Center right away.

If pregnant or breast feeding, ask a doctor before using this product.

Do not use if TAMPER EVIDENT seal around neck of bottle is missing or broken.

OTHER INFORMATION

Store at room temperature.

DIRECTIONS:

Adults and children over 12: Spray twice under the tongue three times per day. For acute symptoms, dosage may be administered up to six times per day.

Children 12 and under: Consult a doctor prior to use.

INACTIVE INGREDIENTS:

Organic alcohol 20% v/v, Purified water.

Keep out of reach of children. In case of overdose, get medical help or call a Poison Control Center right away.

USES:

May temporarily relieve symptoms of feelings of nervous tension and anxiety such as:

- nerves on edge
- stress
- apprehension & worry
- fear & phobias
- occasional sleeplessness**

**Claims based on traditional homeopathic practice, not accepted medical evidence. Not FDA evaluated.

QUESTIONS:

DIST. BY
LIDDELL LABORATORIES INC.
201 APPLE BLVD.
WOODBINE, IA 51579
WWW.LIDDELL.NET
1-800-460-7733

PACKAGE LABEL DISPLAY:

ORAL SPRAYS
LIDDELL
LABORATORIES

EST. 1994
LETTING GO

^51 Anx
Anxiety +
Tension

May relieve symptoms
of anxiety and tension.

HOMEOPATHIC

DOCTOR FORMULATED

...when flower essences
just aren't enough.

1.0 FL OZ (30 ml)